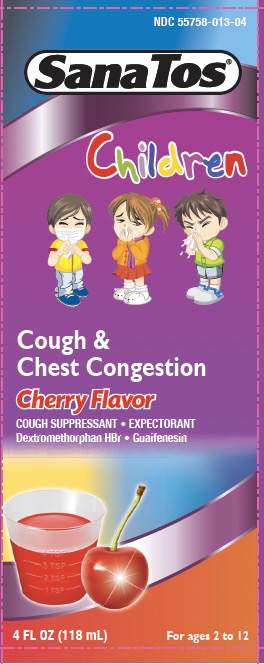 DRUG LABEL: SanaTos Children Cough and Congestion Cherry
NDC: 55758-013 | Form: LIQUID
Manufacturer: Pharmadel LLC
Category: otc | Type: HUMAN OTC DRUG LABEL
Date: 20240502

ACTIVE INGREDIENTS: GUAIFENESIN 100 mg/5 mL; DEXTROMETHORPHAN HYDROBROMIDE 5 mg/5 mL
INACTIVE INGREDIENTS: ANHYDROUS CITRIC ACID; DEXTROSE MONOHYDRATE; D&C RED NO. 33; FD&C RED NO. 40; GLYCERIN; MALTITOL; PROPYLENE GLYCOL; WATER; SACCHARIN SODIUM; SODIUM BENZOATE; SUCRALOSE; XANTHAN GUM

SanaTos Children Cough & Congestion Cherry (APTA)

Active Ingredients & Purposes

PURPOSE

Active Ingredients (in each teaspoonful, 5 mL) | Purposes
Dextromethorphan HBr 5 mg ..... | Cough Suppressant
Guaifenesin 100 mg ..... | Expectorant

Uses

- temporarily relieves cough due to minor throat and bronchial irritation as may occur with a common cold
- helps loosen phlegm (mucus) and thin bronchial secretions to drain the bronchial tubes

Warnings

Do not use

in a child who is taking a prescription monoamine oxidase inhibitor (MAOI) (certain drugs for depression, psychiatric, or emotional conditions, or Parkinson's disease), or for 2 weeks after stopping the MAOI drug. If you do not know if your child's prescription drug contains an MAOI, ask a doctor or pharmacist before giving this product.

Ask a doctor before use, if the child has a

- cough that is accompanied by excessive phlegm (mucus)
- persistent or chronic cough such as occurs with asthma

Stop use and ask a doctor, if the child has a

- cough that lasts more than 7 days, tends to recur, or is accompanied by fever, rash or a persistent headache. These could be signs of a serious condition.

KEEP OUT OF REACH OF CHILDREN.

In case of overdose, get medical help or contact a Poison Control Center right away

Directions

- do not give a child more than 6 doses in any 24-hour period

Age | Dose
Children 6 to under 12 years of age | 1-2 teaspoonfuls (tsps) every 4 hours
Children 2 to under 6 years of age | ½-1 teaspoonful (tsp) every 4 hours
Children under 2 years of age | consult a doctor

Other information

- per teaspoonful (5mL) contains: 3mg Sodium
- store at 20- 25º C (68- 77º F)
- do not refrigerate
- dosage cup included

TAMPER EVIDENT: DO NOT USE IF PRINTED SEAL UNDER CAP IS TORN OR MISSING.

Inactive ingredients

Anhydrous citric acid, D&C red #33, dextrose monohydrate, FD&C red #40, flavors, glycerin, maltitol, propylene glycol, purified water, saccharin sodium, sodium benzoate, sucralose, xanthan gum.

Questions?

1-866-359-3478 (M-F) 9 AM to 5 PM EST or www.pharmadel.com

Distributed by:

PHARMDEL LLC
New Castle, DE 19720